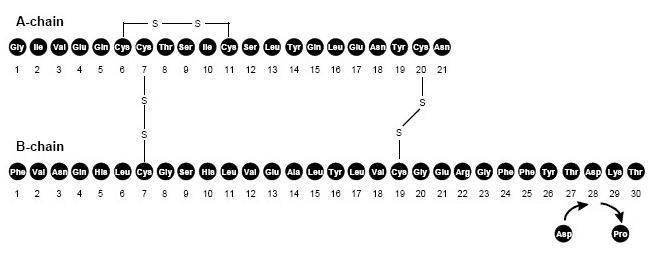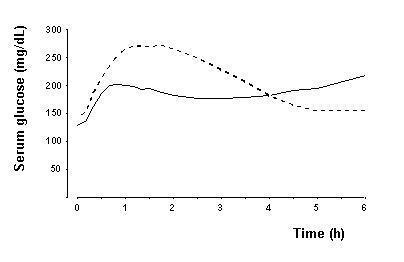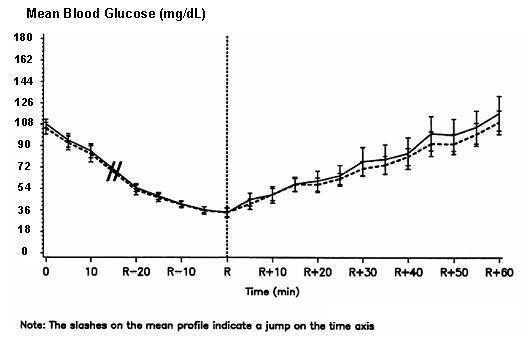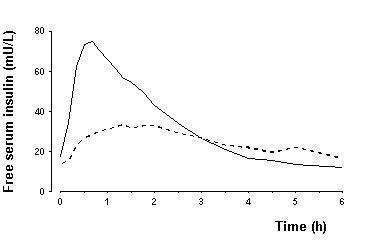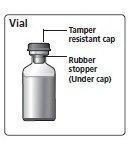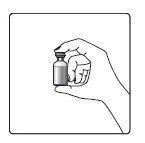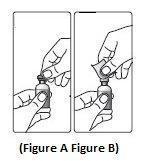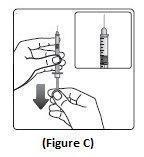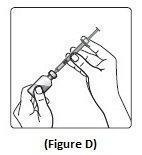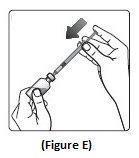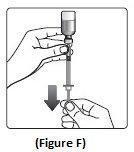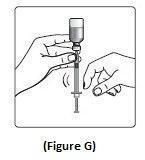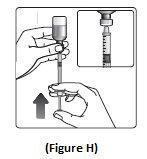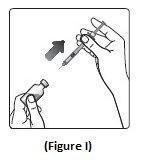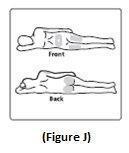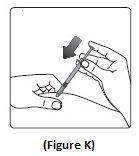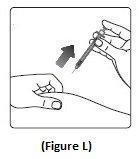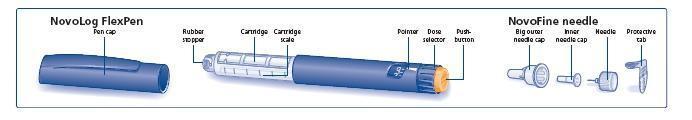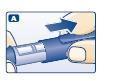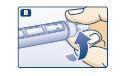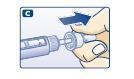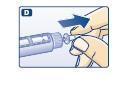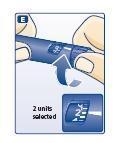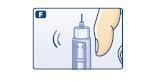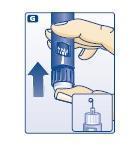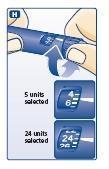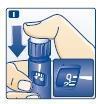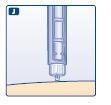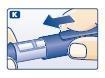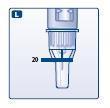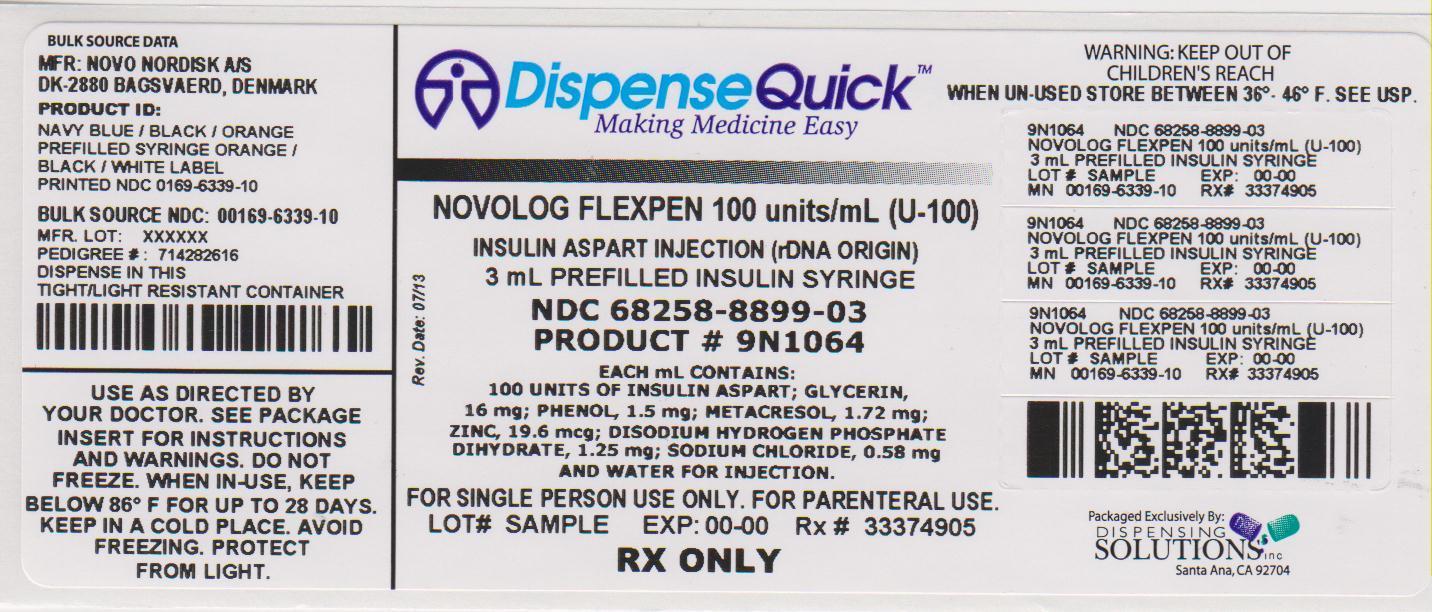 DRUG LABEL: NovoLog
NDC: 68258-8899 | Form: INJECTION, SOLUTION
Manufacturer: Dispensing Solutions, Inc.
Category: prescription | Type: HUMAN PRESCRIPTION DRUG LABEL
Date: 20130723

ACTIVE INGREDIENTS: INSULIN ASPART 100 [iU]/1 mL
INACTIVE INGREDIENTS: SODIUM PHOSPHATE, DIBASIC, DIHYDRATE 1.25 mg/1 mL; GLYCERIN 16 mg/1 mL; HYDROCHLORIC ACID; METACRESOL 1.72 mg/1 mL; PHENOL 1.5 mg/1 mL; SODIUM CHLORIDE 0.58 mg/1 mL; SODIUM HYDROXIDE; ZINC 19.6 ug/1 mL

HIGHLIGHTS OF PRESCRIBING INFORMATION

These highlights do not include all the information needed to use NovoLog safely and effectively.
See full prescribing information for NovoLog.
NovoLog® (insulin aspart [rDNA origin] injection) solution for subcutaneous use
Initial U.S. Approval: 2000

RECENT MAJOR CHANGES

- Warnings and Precautions (5.10) 3/2013

1 INDICATIONS AND USAGE

- NovoLog is an insulin analog indicated to improve glycemic control in adults and children with diabetes mellitus (1.1).

2 DOSAGE AND ADMINISTRATION

- The dosage of NovoLog must be individualized.
- Subcutaneous injection: NovoLog should generally be given immediately (within 5-10 minutes) prior to the start of a meal (2.2).
- Use in pumps: Change the NovoLog in the reservoir at least every 6 days, change the infusion set, and the infusion set insertion site at least every 3 days. NovoLog should not be mixed with other insulins or with a diluent when it is used in the pump (2.3).
- Intravenous use: NovoLog should be used at concentrations from 0.05 U/mL to 1.0 U/mL insulin aspart in infusion systems using polypropylene infusion bags. NovoLog has been shown to be stable in infusion fluids such as 0.9% sodium chloride (2.4).

3 DOSAGE FORMS AND STRENGTHS

Each presentation contains 100 Units of insulin aspart per mL (U-100)

- 10 mL vials (3)
- 3 mL PenFill® cartridges for the 3 mL PenFill cartridge device (3)
- 3 mL NovoLog FlexPen® (3)

4 CONTRAINDICATIONS

- Do not use during episodes of hypoglycemia (4).
- Do not use in patients with hypersensitivity to NovoLog or one of its excipients.

5 WARNINGS AND PRECAUTIONS

- Hypoglycemia is the most common adverse effect of insulin therapy. Glucose monitoring is recommended for all patients with diabetes. Any change of insulin dose should be made cautiously and only under medical supervision (5.1, 5.2).
- Insulin, particularly when given intravenously or in settings of poor glycemic control, can cause hypokalemia. Use caution in patients predisposed to hypokalemia (5.3).
- Like all insulins, NovoLog requirements may be reduced in patients with renal impairment or hepatic impairment (5.4, 5.5).
- Severe, life-threatening, generalized allergy, including anaphylaxis, may occur with insulin products, including NovoLog (5.6).
- Fluid retention and heart failure can occur with concomitant use of thiazolidinediones (TZDs), which are PPAR-gamma agonists, and insulin, including NovoLog (5.10).

6 ADVERSE REACTIONS

Adverse reactions observed with NovoLog include hypoglycemia, allergic reactions, local injection site reactions, lipodystrophy, rash and pruritus (6).

To report SUSPECTED ADVERSE REACTIONS, contact Novo Nordisk Inc. at 1-800-727-6500 or FDA at 1-800-FDA-1088 or www.fda.gov/medwatch.

7 DRUG INTERACTIONS

- The following may increase the blood-glucose-lowering effect and susceptibility to hypoglycemia: oral antidiabetic products, pramlintide, ACE inhibitors, disopyramide, fibrates, fluoxetine, monoamine oxidase inhibitors, propoxyphene, salicylates, somatostatin analogs, sulfonamide antibiotics (7).
- The following may reduce the blood-glucose-lowering effect: corticosteroids, niacin, danazol, diuretics, sympathomimetic agents (e.g., epinephrine, salbutamol, terbutaline), isoniazid, phenothiazine derivatives, somatropin, thyroid hormones, estrogens, progestogens (e.g., in oral contraceptives), atypical antipsychotics (7).
- Beta-blockers, clonidine, lithium salts, and alcohol may either potentiate or weaken the blood-glucose-lowering effect of insulin (7).
- Pentamidine may cause hypoglycemia, which may sometimes be followed by hyperglycemia (7).
- The signs of hypoglycemia may be reduced or absent in patients taking sympatholytic products such as beta-blockers, clonidine, guanethidine, and reserpine (7).

8 USE IN SPECIFIC POPULATIONS

- Pediatric: Has not been studied in children with type 2 diabetes. Has not been studied in children with type 1 diabetes <2 years of age (8.4).

FULL PRESCRIBING INFORMATION

1 INDICATIONS AND USAGE

1.1 Treatment of Diabetes Mellitus

NovoLog is an insulin analog indicated to improve glycemic control in adults and children with diabetes mellitus.

2 DOSAGE AND ADMINISTRATION

2.1 Dosing

NovoLog is an insulin analog with an earlier onset of action than regular human insulin. The dosage of NovoLog must be individualized. NovoLog given by subcutaneous injection should generally be used in regimens with an intermediate or long-acting insulin [see Warnings and Precautions (5), How Supplied/Storage and Handling (16.2)]. The total daily insulin requirement may vary and is usually between 0.5 to 1.0 units/kg/day. When used in a meal-related subcutaneous injection treatment regimen, 50 to 70% of total insulin requirements may be provided by NovoLog and the remainder provided by an intermediate-acting or long-acting insulin. Because of NovoLog’s comparatively rapid onset and short duration of glucose lowering activity, some patients may require more basal insulin and more total insulin to prevent pre-meal hyperglycemia when using NovoLog than when using human regular insulin.

Do not use NovoLog that is viscous (thickened) or cloudy; use only if it is clear and colorless. NovoLog should not be used after the printed expiration date.

2.2 Subcutaneous Injection

NovoLog should be administered by subcutaneous injection in the abdominal region, buttocks, thigh, or upper arm. Because NovoLog has a more rapid onset and a shorter duration of activity than human regular insulin, it should be injected immediately (within 5-10 minutes) before a meal. Injection sites should be rotated within the same region to reduce the risk of lipodystrophy. As with all insulins, the duration of action of NovoLog will vary according to the dose, injection site, blood flow, temperature, and level of physical activity.

NovoLog may be diluted with Insulin Diluting Medium for NovoLog for subcutaneous injection. Diluting one part NovoLog to nine parts diluent will yield a concentration one-tenth that of NovoLog (equivalent to U-10). Diluting one part NovoLog to one part diluent will yield a concentration one-half that of NovoLog (equivalent to U-50).

2.3 Continuous Subcutaneous Insulin Infusion (CSII) by External Pump

NovoLog can also be infused subcutaneously by an external insulin pump [see Warnings and Precautions (5.8, 5.9), How Supplied/Storage and Handling (16.2)]. Diluted insulin should not be used in external insulin pumps. Because NovoLog has a more rapid onset and a shorter duration of activity than human regular insulin, pre-meal boluses of NovoLog should be infused immediately (within 5-10 minutes) before a meal. Infusion sites should be rotated within the same region to reduce the risk of lipodystrophy. The initial programming of the external insulin infusion pump should be based on the total daily insulin dose of the previous regimen. Although there is significant interpatient variability, approximately 50% of the total dose is usually given as meal-related boluses of NovoLog and the remainder is given as a basal infusion. Change the NovoLog in the reservoir at least every 6 days, change the infusion sets and the infusion set insertion site at least every 3 days.

The following insulin pumps† have been used in NovoLog clinical or in vitro studies conducted by Novo Nordisk, the manufacturer of NovoLog:

- Medtronic Paradigm® 512 and 712
- MiniMed 508
- Disetronic® D-TRON® and H-TRON®

Before using a different insulin pump with NovoLog, read the pump label to make sure the pump has been evaluated with NovoLog.

2.4 Intravenous Use

NovoLog can be administered intravenously under medical supervision for glycemic control with close monitoring of blood glucose and potassium levels to avoid hypoglycemia and hypokalemia [see Warnings and Precautions (5), How Supplied/Storage and Handling (16.2)]. For intravenous use, NovoLog should be used at concentrations from 0.05 U/mL to 1.0 U/mL insulin aspart in infusion systems using polypropylene infusion bags. NovoLog has been shown to be stable in infusion fluids such as 0.9% sodium chloride.

Inspect NovoLog for particulate matter and discoloration prior to parenteral administration.

3 DOSAGE FORMS AND STRENGTHS

NovoLog is available in the following package sizes: each presentation contains 100 units of insulin aspart per mL (U-100).

- 10 mL vials
- 3 mL PenFill cartridges for the 3 mL PenFill cartridge delivery device (with or without the addition of a NovoPen® 3 PenMate®) with NovoFine® disposable needles
- 3 mL NovoLog FlexPen

4 CONTRAINDICATIONS

NovoLog is contraindicated

- during episodes of hypoglycemia
- in patients with hypersensitivity to NovoLog or one of its excipients.

5 WARNINGS AND PRECAUTIONS

5.1 Administration

NovoLog has a more rapid onset of action and a shorter duration of activity than regular human insulin. An injection of NovoLog should immediately be followed by a meal within 5-10 minutes. Because of NovoLog’s short duration of action, a longer acting insulin should also be used in patients with type 1 diabetes and may also be needed in patients with type 2 diabetes. Glucose monitoring is recommended for all patients with diabetes and is particularly important for patients using external pump infusion therapy.

Any change of insulin dose should be made cautiously and only under medical supervision. Changing from one insulin product to another or changing the insulin strength may result in the need for a change in dosage. As with all insulin preparations, the time course of NovoLog action may vary in different individuals or at different times in the same individual and is dependent on many conditions, including the site of injection, local blood supply, temperature, and physical activity. Patients who change their level of physical activity or meal plan may require adjustment of insulin dosages. Insulin requirements may be altered during illness, emotional disturbances, or other stresses.

Patients using continuous subcutaneous insulin infusion pump therapy must be trained to administer insulin by injection and have alternate insulin therapy available in case of pump failure.

Needles and NovoLog FlexPen must not be shared.

5.2 Hypoglycemia

Hypoglycemia is the most common adverse effect of all insulin therapies, including NovoLog. Severe hypoglycemia may lead to unconsciousness and/or convulsions and may result in temporary or permanent impairment of brain function or death. Severe hypoglycemia requiring the assistance of another person and/or parenteral glucose infusion or glucagon administration has been observed in clinical trials with insulin, including trials with NovoLog.

The timing of hypoglycemia usually reflects the time-action profile of the administered insulin formulations [see Clinical Pharmacology (12)]. Other factors such as changes in food intake (e.g., amount of food or timing of meals), injection site, exercise, and concomitant medications may also alter the risk of hypoglycemia [see Drug Interactions (7)]. As with all insulins, use caution in patients with hypoglycemia unawareness and in patients who may be predisposed to hypoglycemia (e.g., patients who are fasting or have erratic food intake). The patient’s ability to concentrate and react may be impaired as a result of hypoglycemia. This may present a risk in situations where these abilities are especially important, such as driving or operating other machinery.

Rapid changes in serum glucose levels may induce symptoms of hypoglycemia in persons with diabetes, regardless of the glucose value. Early warning symptoms of hypoglycemia may be different or less pronounced under certain conditions, such as longstanding diabetes, diabetic nerve disease, use of medications such as beta-blockers, or intensified diabetes control [see Drug Interactions (7)]. These situations may result in severe hypoglycemia (and, possibly, loss of consciousness) prior to the patient’s awareness of hypoglycemia. Intravenously administered insulin has a more rapid onset of action than subcutaneously administered insulin, requiring more close monitoring for hypoglycemia.

5.3 Hypokalemia

All insulin products, including NovoLog, cause a shift in potassium from the extracellular to intracellular space, possibly leading to hypokalemia that, if left untreated, may cause respiratory paralysis, ventricular arrhythmia, and death. Use caution in patients who may be at risk for hypokalemia (e.g., patients using potassium-lowering medications, patients taking medications sensitive to serum potassium concentrations, and patients receiving intravenously administered insulin).

5.4 Renal Impairment

As with other insulins, the dose requirements for NovoLog may be reduced in patients with renal impairment [see Clinical Pharmacology (12.3)].

5.5 Hepatic Impairment

As with other insulins, the dose requirements for NovoLog may be reduced in patients with hepatic impairment [see Clinical Pharmacology (12.3)].

5.6 Hypersensitivity and Allergic Reactions

Local Reactions - As with other insulin therapy, patients may experience redness, swelling, or itching at the site of NovoLog injection. These reactions usually resolve in a few days to a few weeks, but in some occasions, may require discontinuation of NovoLog. In some instances, these reactions may be related to factors other than insulin, such as irritants in a skin cleansing agent or poor injection technique. Localized reactions and generalized myalgias have been reported with injected metacresol, which is an excipient in NovoLog.

Systemic Reactions - Severe, life-threatening, generalized allergy, including anaphylaxis, may occur with any insulin product, including NovoLog. Anaphylactic reactions with NovoLog have been reported post-approval. Generalized allergy to insulin may also cause whole body rash (including pruritus), dyspnea, wheezing, hypotension, tachycardia, or diaphoresis. In controlled clinical trials, allergic reactions were reported in 3 of 735 patients (0.4%) treated with regular human insulin and 10 of 1394 patients (0.7%) treated with NovoLog. In controlled and uncontrolled clinical trials, 3 of 2341 (0.1%) NovoLog-treated patients discontinued due to allergic reactions.

5.7 Antibody Production

Increases in anti-insulin antibody titers that react with both human insulin and insulin aspart have been observed in patients treated with NovoLog. Increases in anti-insulin antibodies are observed more frequently with NovoLog than with regular human insulin. Data from a 12-month controlled trial in patients with type 1 diabetes suggest that the increase in these antibodies is transient, and the differences in antibody levels between the regular human insulin and insulin aspart treatment groups observed at 3 and 6 months were no longer evident at 12 months. The clinical significance of these antibodies is not known. These antibodies do not appear to cause deterioration in glycemic control or necessitate increases in insulin dose.

5.8 Mixing of Insulins

- Mixing NovoLog with NPH human insulin immediately before injection attenuates the peak concentration of NovoLog, without significantly affecting the time to peak concentration or total bioavailability of NovoLog. If NovoLog is mixed with NPH human insulin, NovoLog should be drawn into the syringe first, and the mixture should be injected immediately after mixing.
- The efficacy and safety of mixing NovoLog with insulin preparations produced by other manufacturers have not been studied.
- Insulin mixtures should not be administered intravenously.

5.9 Continuous Subcutaneous Insulin Infusion by External Pump

When used in an external subcutaneous insulin infusion pump, NovoLog should not be mixed with any other insulin or diluent. When using NovoLog in an external insulin pump, the NovoLog-specific information should be followed (e.g., in-use time, frequency of changing infusion sets) because NovoLog-specific information may differ from general pump manual instructions.

Pump or infusion set malfunctions or insulin degradation can lead to a rapid onset of hyperglycemia and ketosis because of the small subcutaneous depot of insulin. This is especially pertinent for rapid-acting insulin analogs that are more rapidly absorbed through skin and have a shorter duration of action. Prompt identification and correction of the cause of hyperglycemia or ketosis is necessary. Interim therapy with subcutaneous injection may be required [see Dosage and Administration (2.3), Warnings and Precautions (5.8, 5.9), How Supplied/Storage and Handling (16.2), and Patient Counseling Information (17.2)].

NovoLog should not be exposed to temperatures greater than 37°C (98.6°F). NovoLog that will be used in a pump should not be mixed with other insulin or with a diluent [see Dosage and Administration (2.3), Warnings and Precautions (5.8, 5.9), How Supplied/Storage and Handling (16.2), and Patient Counseling Information (17.2)].

5.10 Fluid retention and heart failure with concomitant use of PPAR-gamma agonists

Thiazolidinediones (TZDs), which are peroxisome proliferator-activated receptor (PPAR)-gamma agonists, can cause dose-related fluid retention, particularly when used in combination with insulin. Fluid retention may lead to or exacerbate heart failure. Patients treated with insulin, including NovoLog, and a PPAR-gamma agonist should be observed for signs and symptoms of heart failure. If heart failure develops, it should be managed according to current standards of care, and discontinuation or dose reduction of the PPAR-gamma agonist must be considered.

6 ADVERSE REACTIONS

Clinical Trial Experience

Because clinical trials are conducted under widely varying designs, the adverse reaction rates reported in one clinical trial may not be easily compared to those rates reported in another clinical trial, and may not reflect the rates actually observed in clinical practice.

- Hypoglycemia

Hypoglycemia is the most commonly observed adverse reaction in patients using insulin, including NovoLog [see Warnings and Precautions (5)].

- Insulin initiation and glucose control intensification

Intensification or rapid improvement in glucose control has been associated with a transitory, reversible ophthalmologic refraction disorder, worsening of diabetic retinopathy, and acute painful peripheral neuropathy. However, long-term glycemic control decreases the risk of diabetic retinopathy and neuropathy.

- Lipodystrophy

Long-term use of insulin, including NovoLog, can cause lipodystrophy at the site of repeated insulin injections or infusion. Lipodystrophy includes lipohypertrophy (thickening of adipose tissue) and lipoatrophy (thinning of adipose tissue), and may affect insulin absorption. Rotate insulin injection or infusion sites within the same region to reduce the risk of lipodystrophy.

- Weight gain

Weight gain can occur with some insulin therapies, including NovoLog, and has been attributed to the anabolic effects of insulin and the decrease in glucosuria.

- Peripheral Edema

Insulin may cause sodium retention and edema, particularly if previously poor metabolic control is improved by intensified insulin therapy.

- Frequencies of adverse drug reactions

The frequencies of adverse drug reactions during NovoLog clinical trials in patients with type 1 diabetes mellitus and type 2 diabetes mellitus are listed in the tables below.

Table 1: Treatment-Emergent Adverse Events in Patients with Type 1 Diabetes Mellitus (Adverse events with frequency ≥ 5% and occurring more frequently with NovoLog compared to human regular insulin are listed)
 | NovoLog + NPH; N= 596 |  | Human Regular Insulin + NPH; N= 286
Preferred Term | N | (%) | N | (%)
Hypoglycemia [Hypoglycemia is defined as an episode of blood glucose concentration <45 mg/dL, with or without symptoms. See Section 14 for the incidence of serious hypoglycemia in the individual clinical trials.] | 448 | 75% | 205 | 72%
Headache | 70 | 12% | 28 | 10%
Injury accidental | 65 | 11% | 29 | 10%
Nausea | 43 | 7% | 13 | 5%
Diarrhea | 28 | 5% | 9 | 3%

Table 2: Treatment-Emergent Adverse Events in Patients with Type 2 Diabetes Mellitus (except for hypoglycemia, adverse events with frequency ≥ 5% and occurring more frequently with NovoLog compared to human regular insulin are listed)
 | NovoLog + NPH; N= 91 |  | Human Regular Insulin + NPH; N= 91
 | N | (%) | N | (%)
Hypoglycemia [Hypoglycemia is defined as an episode of blood glucose concentration <45 mg/dL, with or without symptoms. See Section 14 for the incidence of serious hypoglycemia in the individual clinical trials.] | 25 | 27% | 33 | 36%
Hyporeflexia | 10 | 11% | 6 | 7%
Onychomycosis | 9 | 10% | 5 | 5%
Sensory disturbance | 8 | 9% | 6 | 7%
Urinary tract infection | 7 | 8% | 6 | 7%
Chest pain | 5 | 5% | 3 | 3%
Headache | 5 | 5% | 3 | 3%
Skin disorder | 5 | 5% | 2 | 2%
Abdominal pain | 5 | 5% | 1 | 1%
Sinusitis | 5 | 5% | 1 | 1%

Postmarketing Data

The following additional adverse reactions have been identified during postapproval use of NovoLog. Because these adverse reactions are reported voluntarily from a population of uncertain size, it is generally not possible to reliably estimate their frequency. Medication errors in which other insulins have been accidentally substituted for NovoLog have been identified during postapproval use [see Patient Counseling Information (17)].

7 DRUG INTERACTIONS

A number of substances affect glucose metabolism and may require insulin dose adjustment and particularly close monitoring.

- The following are examples of substances that may increase the blood-glucose-lowering effect and susceptibility to hypoglycemia: oral antidiabetic products, pramlintide, ACE inhibitors, disopyramide, fibrates, fluoxetine, monoamine oxidase (MAO) inhibitors, propoxyphene, salicylates, somatostatin analog (e.g., octreotide), sulfonamide antibiotics.
- The following are examples of substances that may reduce the blood-glucose-lowering effect: corticosteroids, niacin, danazol, diuretics, sympathomimetic agents (e.g., epinephrine, salbutamol, terbutaline), isoniazid, phenothiazine derivatives, somatropin, thyroid hormones, estrogens, progestogens (e.g., in oral contraceptives), atypical antipsychotics.
- Beta-blockers, clonidine, lithium salts, and alcohol may either potentiate or weaken the blood-glucose-lowering effect of insulin.
- Pentamidine may cause hypoglycemia, which may sometimes be followed by hyperglycemia.
- The signs of hypoglycemia may be reduced or absent in patients taking sympatholytic products such as beta-blockers, clonidine, guanethidine, and reserpine.

8 USE IN SPECIFIC POPULATIONS

8.1 Pregnancy

Pregnancy Category B. All pregnancies have a background risk of birth defects, loss, or other adverse outcome regardless of drug exposure. This background risk is increased in pregnancies complicated by hyperglycemia and may be decreased with good metabolic control. It is essential for patients with diabetes or history of gestational diabetes to maintain good metabolic control before conception and throughout pregnancy. Insulin requirements may decrease during the first trimester, generally increase during the second and third trimesters, and rapidly decline after delivery. Careful monitoring of glucose control is essential in these patients. Therefore, female patients should be advised to tell their physician if they intend to become, or if they become pregnant while taking NovoLog.

An open-label, randomized study compared the safety and efficacy of NovoLog (n=157) versus regular human insulin (n=165) in 322 pregnant women with type 1 diabetes. Two-thirds of the enrolled patients were already pregnant when they entered the study. Because only one-third of the patients enrolled before conception, the study was not large enough to evaluate the risk of congenital malformations. Both groups achieved a mean HbA1c of ~ 6% during pregnancy, and there was no significant difference in the incidence of maternal hypoglycemia.

Subcutaneous reproduction and teratology studies have been performed with NovoLog and regular human insulin in rats and rabbits. In these studies, NovoLog was given to female rats before mating, during mating, and throughout pregnancy, and to rabbits during organogenesis. The effects of NovoLog did not differ from those observed with subcutaneous regular human insulin. NovoLog, like human insulin, caused pre- and post-implantation losses and visceral/skeletal abnormalities in rats at a dose of 200 U/kg/day (approximately 32 times the human subcutaneous dose of 1.0 U/kg/day, based on U/body surface area) and in rabbits at a dose of 10 U/kg/day (approximately three times the human subcutaneous dose of 1.0 U/kg/day, based on U/body surface area). The effects are probably secondary to maternal hypoglycemia at high doses. No significant effects were observed in rats at a dose of 50 U/kg/day and in rabbits at a dose of 3 U/kg/day. These doses are approximately 8 times the human subcutaneous dose of 1.0 U/kg/day for rats and equal to the human subcutaneous dose of 1.0 U/kg/day for rabbits, based on U/body surface area.

8.3 Nursing Mothers

It is unknown whether insulin aspart is excreted in human milk. Use of NovoLog is compatible with breastfeeding, but women with diabetes who are lactating may require adjustments of their insulin doses.

8.4 Pediatric Use

NovoLog is approved for use in children for subcutaneous daily injections and for subcutaneous continuous infusion by external insulin pump. NovoLog has not been studied in pediatric patients younger than 2 years of age. NovoLog has not been studied in pediatric patients with type 2 diabetes. Please see Section 14 CLINICAL STUDIES for summaries of clinical studies.

8.5 Geriatric Use

Of the total number of patients (n= 1,375) treated with NovoLog in 3 controlled clinical studies, 2.6% (n=36) were 65 years of age or over. One-half of these patients had type 1 diabetes (18/1285) and the other half had type 2 diabetes (18/90). The HbA1c response to NovoLog, as compared to human insulin, did not differ by age, particularly in patients with type 2 diabetes. Additional studies in larger populations of patients 65 years of age or over are needed to permit conclusions regarding the safety of NovoLog in elderly compared to younger patients. Pharmacokinetic/pharmacodynamic studies to assess the effect of age on the onset of NovoLog action have not been performed.

10 OVERDOSAGE

Excess insulin administration may cause hypoglycemia and, particularly when given intravenously, hypokalemia. Mild episodes of hypoglycemia usually can be treated with oral glucose. Adjustments in drug dosage, meal patterns, or exercise, may be needed. More severe episodes with coma, seizure, or neurologic impairment may be treated with intramuscular/subcutaneous glucagon or concentrated intravenous glucose. Sustained carbohydrate intake and observation may be necessary because hypoglycemia may recur after apparent clinical recovery. Hypokalemia must be corrected appropriately.

11 DESCRIPTION

NovoLog (insulin aspart [rDNA origin] injection) is a rapid-acting human insulin analog used to lower blood glucose. NovoLog is homologous with regular human insulin with the exception of a single substitution of the amino acid proline by aspartic acid in position B28, and is produced by recombinant DNA technology utilizing Saccharomyces cerevisiae (baker's yeast). Insulin aspart has the empirical formula C256H381N65079S6 and a molecular weight of 5825.8.

Figure 1. Structural formula of insulin aspart.

NovoLog is a sterile, aqueous, clear, and colorless solution, that contains insulin aspart 100 Units/mL, glycerin 16 mg/mL, phenol 1.50 mg/mL, metacresol 1.72 mg/mL, zinc 19.6 mcg/mL, disodium hydrogen phosphate dihydrate 1.25 mg/mL, sodium chloride 0.58 mg/mL and water for injection. NovoLog has a pH of 7.2-7.6. Hydrochloric acid 10% and/or sodium hydroxide 10% may be added to adjust pH.

12 CLINICAL PHARMACOLOGY

12.1 Mechanism of Action

The primary activity of NovoLog is the regulation of glucose metabolism. Insulins, including NovoLog, bind to the insulin receptors on muscle and fat cells and lower blood glucose by facilitating the cellular uptake of glucose and simultaneously inhibiting the output of glucose from the liver.

12.2 Pharmacodynamics

Studies in normal volunteers and patients with diabetes demonstrated that subcutaneous administration of NovoLog has a more rapid onset of action than regular human insulin.

In a study in patients with type 1 diabetes (n=22), the maximum glucose-lowering effect of NovoLog occurred between 1 and 3 hours after subcutaneous injection (see Figure 2). The duration of action for NovoLog is 3 to 5 hours. The time course of action of insulin and insulin analogs such as NovoLog may vary considerably in different individuals or within the same individual. The parameters of NovoLog activity (time of onset, peak time and duration) as designated in Figure 2 should be considered only as general guidelines. The rate of insulin absorption and onset of activity is affected by the site of injection, exercise, and other variables [see Warnings and Precautions (5.1)].

Figure 2. Serial mean serum glucose collected up to 6 hours following a single pre-meal dose of NovoLog (solid curve) or regular human insulin (hatched curve) injected immediately before a meal in 22 patients with type 1 diabetes.

A double-blind, randomized, two-way cross-over study in 16 patients with type 1 diabetes demonstrated that intravenous infusion of NovoLog resulted in a blood glucose profile that was similar to that after intravenous infusion with regular human insulin. NovoLog or human insulin was infused until the patient’s blood glucose decreased to 36 mg/dL, or until the patient demonstrated signs of hypoglycemia (rise in heart rate and onset of sweating), defined as the time of autonomic reaction (R) (see Figure 3).

Figure 3. Mean blood glucose profiles following intravenous infusion of NovoLog (hatched curve) and regular human insulin (solid curve) in 16 patients with type 1 diabetes. R represents the time of autonomic reaction.

12.3 Pharmacokinetics

The single substitution of the amino acid proline with aspartic acid at position B28 in NovoLog reduces the molecule's tendency to form hexamers as observed with regular human insulin. NovoLog is, therefore, more rapidly absorbed after subcutaneous injection compared to regular human insulin.

In a randomized, double-blind, crossover study 17 healthy Caucasian male subjects between 18 and 40 years of age received an intravenous infusion of either NovoLog or regular human insulin at 1.5 mU/kg/min for 120 minutes. The mean insulin clearance was similar for the two groups with mean values of 1.2 l/h/kg for the NovoLog group and 1.2 l/h/kg for the regular human insulin group.

Bioavailability and Absorption - NovoLog has a faster absorption, a faster onset of action, and a shorter duration of action than regular human insulin after subcutaneous injection (see Figure 2 and Figure 4). The relative bioavailability of NovoLog compared to regular human insulin indicates that the two insulins are absorbed to a similar extent.

Figure 4. Serial mean serum free insulin concentration collected up to 6 hours following a single pre-meal dose of NovoLog (solid curve) or regular human insulin (hatched curve) injected immediately before a meal in 22 patients with type 1 diabetes.

In studies in healthy volunteers (total n=107) and patients with type 1 diabetes (total n=40), NovoLog consistently reached peak serum concentrations approximately twice as fast as regular human insulin. The median time to maximum concentration in these trials was 40 to 50 minutes for NovoLog versus 80 to 120 minutes for regular human insulin. In a clinical trial in patients with type 1 diabetes, NovoLog and regular human insulin, both administered subcutaneously at a dose of 0.15 U/kg body weight, reached mean maximum concentrations of 82 and 36 mU/L, respectively. Pharmacokinetic/pharmacodynamic characteristics of insulin aspart have not been established in patients with type 2 diabetes.

The intra-individual variability in time to maximum serum insulin concentration for healthy male volunteers was significantly less for NovoLog than for regular human insulin. The clinical significance of this observation has not been established.

In a clinical study in healthy non-obese subjects, the pharmacokinetic differences between NovoLog and regular human insulin described above, were observed independent of the site of injection (abdomen, thigh, or upper arm).

Distribution and Elimination - NovoLog has low binding to plasma proteins (<10%), similar to that seen with regular human insulin. After subcutaneous administration in normal male volunteers (n=24), NovoLog was more rapidly eliminated than regular human insulin with an average apparent half-life of 81 minutes compared to 141 minutes for regular human insulin.

Specific Populations

Children and Adolescents - The pharmacokinetic and pharmacodynamic properties of NovoLog and regular human insulin were evaluated in a single dose study in 18 children (6-12 years, n=9) and adolescents (13-17 years [Tanner grade > 2], n=9) with type 1 diabetes. The relative differences in pharmacokinetics and pharmacodynamics in children and adolescents with type 1 diabetes between NovoLog and regular human insulin were similar to those in healthy adult subjects and adults with type 1 diabetes.

Gender - In healthy volunteers, no difference in insulin aspart levels was seen between men and women when body weight differences were taken into account. There was no significant difference in efficacy noted (as assessed by HbAlc) between genders in a trial in patients with type 1 diabetes.

Obesity - A single subcutaneous dose of 0.1 U/kg NovoLog was administered in a study of 23 patients with type 1 diabetes and a wide range of body mass index (BMI, 22-39 kg/m^2). The pharmacokinetic parameters, AUC and Cmax, of NovoLog were generally unaffected by BMI in the different groups – BMI 19-23 kg/m^2 (N=4); BMI 23-27 kg/m^2 (N=7); BMI 27-32 kg/m^2 (N=6) and BMI >32 kg/m^2 (N=6). Clearance of NovoLog was reduced by 28% in patients with BMI >32 kg/m^2 compared to patients with BMI <23 kg/m^2.

Renal Impairment - Some studies with human insulin have shown increased circulating levels of insulin in patients with renal failure. A single subcutaneous dose of 0.08 U/kg NovoLog was administered in a study to subjects with either normal (N=6) creatinine clearance (CLcr) (> 80 ml/min) or mild (N=7; CLcr = 50-80 ml/min), moderate (N=3; CLcr = 30-50 ml/min) or severe (but not requiring hemodialysis) (N=2; CLcr = <30 ml/min) renal impairment. In this small study, there was no apparent effect of creatinine clearance values on AUC and Cmax of NovoLog. Careful glucose monitoring and dose adjustments of insulin, including NovoLog, may be necessary in patients with renal dysfunction [see Warnings and Precautions (5.4)].

Hepatic Impairment - Some studies with human insulin have shown increased circulating levels of insulin in patients with liver failure. A single subcutaneous dose of 0.06 U/kg NovoLog was administered in an open-label, single-dose study of 24 subjects (N=6/group) with different degree of hepatic impairment (mild, moderate and severe) having Child-Pugh Scores ranging from 0 (healthy volunteers) to 12 (severe hepatic impairment). In this small study, there was no correlation between the degree of hepatic failure and any NovoLog pharmacokinetic parameter. Careful glucose monitoring and dose adjustments of insulin, including NovoLog, may be necessary in patients with hepatic dysfunction [see Warnings and Precautions (5.5)].

The effect of age, ethnic origin, pregnancy and smoking on the pharmacokinetics and pharmacodynamics of NovoLog has not been studied.

13 NONCLINICAL TOXICOLOGY

13.1 Carcinogenesis, Mutagenesis, Impairment of Fertility

Standard 2-year carcinogenicity studies in animals have not been performed to evaluate the carcinogenic potential of NovoLog. In 52-week studies, Sprague-Dawley rats were dosed subcutaneously with NovoLog at 10, 50, and 200 U/kg/day (approximately 2, 8, and 32 times the human subcutaneous dose of 1.0 U/kg/day, based on U/body surface area, respectively). At a dose of 200 U/kg/day, NovoLog increased the incidence of mammary gland tumors in females when compared to untreated controls. The incidence of mammary tumors for NovoLog was not significantly different than for regular human insulin. The relevance of these findings to humans is not known. NovoLog was not genotoxic in the following tests: Ames test, mouse lymphoma cell forward gene mutation test, human peripheral blood lymphocyte chromosome aberration test, in vivo micronucleus test in mice, and in ex vivo UDS test in rat liver hepatocytes. In fertility studies in male and female rats, at subcutaneous doses up to 200 U/kg/day (approximately 32 times the human subcutaneous dose, based on U/body surface area), no direct adverse effects on male and female fertility, or general reproductive performance of animals was observed.

13.2 Animal Toxicology and/or Pharmacology

In standard biological assays in mice and rabbits, one unit of NovoLog has the same glucose-lowering effect as one unit of regular human insulin. In humans, the effect of NovoLog is more rapid in onset and of shorter duration, compared to regular human insulin, due to its faster absorption after subcutaneous injection (see Section 12 CLINICAL PHARMACOLOGY Figure 2 and Figure 4).

14 CLINICAL STUDIES

14.1 Subcutaneous Daily Injections

Two six-month, open-label, active-controlled studies were conducted to compare the safety and efficacy of NovoLog to Novolin R in adult patients with type 1 diabetes. Because the two study designs and results were similar, data are shown for only one study (see Table 3). NovoLog was administered by subcutaneous injection immediately prior to meals and regular human insulin was administered by subcutaneous injection 30 minutes before meals. NPH insulin was administered as the basal insulin in either single or divided daily doses. Changes in HbA1c and the incidence rates of severe hypoglycemia (as determined from the number of events requiring intervention from a third party) were comparable for the two treatment regimens in this study (Table 3) as well as in the other clinical studies that are cited in this section. Diabetic ketoacidosis was not reported in any of the adult studies in either treatment group.

Table 3. Subcutaneous NovoLog Administration in Type 1 Diabetes (24 weeks; n=882)
 | NovoLog + NPH | Novolin R + NPH
N | 596 | 286
Baseline HbA1c (%) [Values are Mean ± SD] | 7.9 ±1.1 | 8.0 ± 1.2
Change from Baseline HbA1c (%) | -0.1 ± 0.8 | 0.0 ± 0.8
Treatment Difference in HbA1c , Mean (95% confidence interval) | -0.2 (-0.3, -0.1)
Baseline insulin dose (IU/kg/24 hours) | 0.7 ± 0.2 | 0.7 ± 0.2
End-of-Study insulin dose (IU/kg/24 hours) | 0.7 ± 0.2 | 0.7 ± 0.2
Patients with severe hypoglycemia (n, %) [Severe hypoglycemia refers to hypoglycemia associated with central nervous system symptoms and requiring the intervention of another person or hospitalization.] | 104 (17%) | 54 (19%)
Baseline body weight (kg); Weight Change from baseline (kg) | 75.3 ± 14.5; 0.5 ± 3.3 | 75.9 ± 13.1; 0.9 ± 2.9

A 24-week, parallel-group study of children and adolescents with type 1 diabetes (n = 283) aged 6 to 18 years compared two subcutaneous multiple-dose treatment regimens: NovoLog (n = 187) or Novolin R (n = 96). NPH insulin was administered as the basal insulin. NovoLog achieved glycemic control comparable to Novolin R, as measured by change in HbA1c (Table 4) and both treatment groups had a comparable incidence of hypoglycemia. Subcutaneous administration of NovoLog and regular human insulin have also been compared in children with type 1 diabetes (n=26) aged 2 to 6 years with similar effects on HbA1c and hypoglycemia.

Table 4. Pediatric Subcutaneous Administration of NovoLog in Type 1 Diabetes (24 weeks; n=283)
 | NovoLog + NPH | Novolin R + NPH
N | 187 | 96
Baseline HbA1c (%) [Values are Mean ± SD] | 8.3 ± 1.2 | 8.3 ± 1.3
Change from Baseline HbA1c (%) | 0.1± 1.0 | 0.1± 1.1
Treatment Difference in HbA1c, Mean (95% confidence interval) | 0.1 (-0.5, 0.1)
Baseline insulin dose (IU/kg/24 hours) | 0.4 ± 0.2 | 0.6 ± 0.2
End-of-Study insulin dose (IU/kg/24 hours) | 0.4 ± 0.2 | 0.7 ± 0.2
Patients with severe hypoglycemia (n, %) [Severe hypoglycemia refers to hypoglycemia associated with central nervous system symptoms and requiring the intervention of another person or hospitalization.] | 11 (6%) | 9 (9%)
Diabetic ketoacidosis (n, %) | 10 (5%) | 2 (2%)
Baseline body weight (kg); Weight Change from baseline (kg) | 50.6 ± 19.6; 2.7 ± 3.5 | 48.7 ± 15.8; 2.4 ± 2.6

One six-month, open-label, active-controlled study was conducted to compare the safety and efficacy of NovoLog to Novolin R in patients with type 2 diabetes (Table 5). NovoLog was administered by subcutaneous injection immediately prior to meals and regular human insulin was administered by subcutaneous injection 30 minutes before meals. NPH insulin was administered as the basal insulin in either single or divided daily doses. Changes in HbAlc and the rates of severe hypoglycemia (as determined from the number of events requiring intervention from a third party) were comparable for the two treatment regimens.

Table 5. Subcutaneous NovoLog Administration in Type 2 Diabetes (6 months; n=176)
 | NovoLog + NPH | Novolin R + NPH
N | 90 | 86
Baseline HbA1c (%) [Values are Mean ± SD] | 8.1 ± 1.2 | 7.8 ± 1.1
Change from Baseline HbA1c (%) | -0.3 ± 1.0 | -0.1 ± 0.8
Treatment Difference in HbA1c, Mean (95% confidence interval) | - 0.1 (-0.4, -0.1)
Baseline insulin dose (IU/kg/24 hours) | 0.6 ± 0.3 | 0.6 ± 0.3
End-of-Study insulin dose (IU/kg/24 hours) | 0.7 ± 0.3 | 0.7 ± 0.3
Patients with severe hypoglycemia (n, %) [Severe hypoglycemia refers to hypoglycemia associated with central nervous system symptoms and requiring the intervention of another person or hospitalization.] | 9 (10%) | 5 (8%)
Baseline body weight (kg); Weight Change from baseline (kg) | 88.4 ± 13.3; 1.2 ± 3.0 | 85.8 ± 14.8; 0.4 ± 3.1

14.2 Continuous Subcutaneous Insulin Infusion (CSII) by External Pump

Two open-label, parallel design studies (6 weeks [n=29] and 16 weeks [n=118]) compared NovoLog to buffered regular human insulin (Velosulin) in adults with type 1 diabetes receiving a subcutaneous infusion with an external insulin pump. The two treatment regimens had comparable changes in HbA1c and rates of severe hypoglycemia.

Table 6. Adult Insulin Pump Study in Type 1 Diabetes (16 weeks; n=118)
 | NovoLog | Buffered human insulin
N | 59 | 59
Baseline HbA1c (%) [Values are Mean ± SD] | 7.3 ± 0.7 | 7.5 ± 0.8
Change from Baseline HbA1c (%) | 0.0 ± 0.5 | 0.2 ± 0.6
Treatment Difference in HbA1c, Mean (95% confidence interval) | 0.3 (-0.1, 0.4)
Baseline insulin dose (IU/kg/24 hours) | 0.7 ± 0.8 | 0.6 ± 0.2
End-of-Study insulin dose (IU/kg/24 hours) | 0.7 ± 0.7 | 0.6 ± 0.2
Patients with severe hypoglycemia (n, %) [Severe hypoglycemia refers to hypoglycemia associated with central nervous system symptoms and requiring the intervention of another person or hospitalization.] | 1 (2%) | 2 (3%)
Baseline body weight (kg); Weight Change from baseline (kg) | 77.4 ± 16.1; 0.1 ± 3.5 | 74.8 ± 13.8; -0.0 ± 1.7

A randomized, 16-week, open-label, parallel design study of children and adolescents with type 1 diabetes (n=298) aged 4-18 years compared two subcutaneous infusion regimens administered via an external insulin pump: NovoLog (n=198) or insulin lispro (n=100). These two treatments resulted in comparable changes from baseline in HbA1c and comparable rates of hypoglycemia after 16 weeks of treatment (see Table 7).

Table 7. Pediatric Insulin Pump Study in Type 1 Diabetes (16 weeks; n=298)
 | NovoLog | Lispro
N | 198 | 100
Baseline HbA1c (%) [Values are Mean ± SD] | 8.0 ± 0.9 | 8.2 ± 0.8
Change from Baseline HbA1c (%) | -0.1 ± 0.8 | -0.1 ± 0.7
Treatment Difference in HbA1c, Mean (95% confidence interval) | -0.1 (-0.3, 0.1)
Baseline insulin dose (IU/kg/24 hours) | 0.9 ± 0.3 | 0.9 ± 0.3
End-of-Study insulin dose (IU/kg/24 hours) | 0.9 ± 0.2 | 0.9 ± 0.2
Patients with severe hypoglycemia (n, %) [Severe hypoglycemia refers to hypoglycemia associated with central nervous system symptoms and requiring the intervention of another person or hospitalization.] | 19 (10%) | 8 (8%)
Diabetic ketoacidosis (n, %) | 1 (0.5%) | 0 (0)
Baseline body weight (kg); Weight Change from baseline (kg) | 54.1 ± 19.7; 1.8 ± 2.1 | 55.5 ± 19.0; 1.6 ± 2.1

An open-label, 16-week parallel design trial compared pre-prandial NovoLog injection in conjunction with NPH injections to NovoLog administered by continuous subcutaneous infusion in 127 adults with type 2 diabetes. The two treatment groups had similar reductions in HbA1c and rates of severe hypoglycemia (Table 8) [see Indications and Usage (1), Dosage and Administration (2), Warnings and Precautions (5) and How Supplied/Storage and Handling (16.2)].

Table 8. Pump Therapy in Type 2 Diabetes (16 weeks; n=127)
 | NovoLog pump | NovoLog + NPH
N | 66 | 61
Baseline HbA1c (%) [Values are Mean ± SD] | 8.2 ± 1.4 | 8.0 ± 1.1
Change from Baseline HbA1c (%) | -0.6 ± 1.1 | -0.5 ± 0.9
Treatment Difference in HbA1c, Mean (95% confidence interval) | 0.1 (0.4, 0.3)
Baseline insulin dose (IU/kg/24 hours) | 0.7 ± 0.3 | 0.8 ± 0.5
End-of-Study insulin dose (IU/kg/24 hours) | 0.9 ± 0.4 | 0.9 ± 0.5
Baseline body weight (kg); Weight Change from baseline (kg) | 96.4 ± 17.0; 1.7 ± 3.7 | 96.9 ± 17.9; 0.7 ± 4.1

14.3 Intravenous Administration of NovoLog

See Section 12.2 CLINICAL PHARMACOLOGY/Pharmacodynamics.

16 HOW SUPPLIED/STORAGE AND HANDLING

16.1 How Supplied

NovoLog is available in the following package sizes: each presentation containing 100 Units of insulin aspart per mL (U-100).

10 mL vials | NDC 0169-7501-11
3 mL PenFill cartridges [NovoLog PenFill cartridges are designed for use with Novo Nordisk 3 mL PenFill cartridge compatible insulin delivery devices (with or without the addition of a NovoPen 3 PenMate) with NovoFine disposable needles.] | NDC 0169-3303-12
3 mL NovoLog FlexPen | NDC 0169-6339-10

16.2 Recommended Storage

Unused NovoLog should be stored in a refrigerator between 2° and 8°C (36° to 46°F). Do not store in the freezer or directly adjacent to the refrigerator cooling element. Do not freeze NovoLog and do not use NovoLog if it has been frozen. NovoLog should not be drawn into a syringe and stored for later use.

Vials: After initial use a vial may be kept at temperatures below 30°C (86°F) for up to 28 days, but should not be exposed to excessive heat or sunlight. Opened vials may be refrigerated.

Unpunctured vials can be used until the expiration date printed on the label if they are stored in a refrigerator. Keep unused vials in the carton so they will stay clean and protected from light.

PenFill cartridges or NovoLog FlexPen:

Once a cartridge or a NovoLog FlexPen is punctured, it should be kept at temperatures below 30°C (86°F) for up to 28 days, but should not be exposed to excessive heat or sunlight. A NovoLog FlexPen or cartridge in use must NOT be stored in the refrigerator. Keep the NovoLog FlexPen and all PenFill cartridges away from direct heat and sunlight. Unpunctured NovoLog FlexPen and PenFill cartridges can be used until the expiration date printed on the label if they are stored in a refrigerator. Keep unused NovoLog FlexPen and PenFill cartridges in the carton so they will stay clean and protected from light.

Always remove the needle after each injection and store the 3 mL PenFill cartridge delivery device or NovoLog FlexPen without a needle attached. This prevents contamination and/or infection, or leakage of insulin, and will ensure accurate dosing. Always use a new needle for each injection to prevent contamination.

Pump:

NovoLog in the pump reservoir should be discarded after at least every 6 days of use or after exposure to temperatures that exceed 37°C (98.6°F). The infusion set and the infusion set insertion site should be changed at least every 3 days.

Summary of Storage Conditions:

The storage conditions are summarized in the following table:

Table 9. Storage conditions for vial, PenFill cartridges and NovoLog FlexPen
NovoLog; presentation | Not in-use (unopened) Room Temperature (below 30°C) | Not in-use (unopened) Refrigerated | In-use (opened) Room Temperature (below 30°C)
10 mL vial | 28 days | Until expiration date | 28 days (refrigerated/room temperature)
3 mL PenFill cartridges | 28 days | Until expiration date | 28 days; (Do not refrigerate)
3 mL NovoLog FlexPen | 28 days | Until expiration date | 28 days; (Do not refrigerate)

Storage of Diluted NovoLog

NovoLog diluted with Insulin Diluting Medium for NovoLog to a concentration equivalent to U-10 or equivalent to U-50 may remain in patient use at temperatures below 30°C (86°F) for 28 days.

Storage of NovoLog in Infusion Fluids

Infusion bags prepared as indicated under Dosage and Administration (2) are stable at room temperature for 24 hours. Some insulin will be initially adsorbed to the material of the infusion bag.

17 PATIENT COUNSELING INFORMATION

[See FDA-Approved Patient Labeling (17.3)]

17.1 Physician Instructions

Maintenance of normal or near-normal glucose control is a treatment goal in diabetes mellitus and has been associated with a reduction in diabetic complications. Patients should be informed about potential risks and benefits of NovoLog therapy including the possible adverse reactions. Patients should also be offered continued education and advice on insulin therapies, injection technique, life-style management, regular glucose monitoring, periodic glycosylated hemoglobin testing, recognition and management of hypo- and hyperglycemia, adherence to meal planning, complications of insulin therapy, timing of dose, instruction in the use of injection or subcutaneous infusion devices, and proper storage of insulin. Patients should be informed that frequent, patient-performed blood glucose measurements are needed to achieve optimal glycemic control and avoid both hyper- and hypoglycemia.

The patient’s ability to concentrate and react may be impaired as a result of hypoglycemia. This may present a risk in situations where these abilities are especially important, such as driving or operating other machinery. Patients who have frequent hypoglycemia or reduced or absent warning signs of hypoglycemia should be advised to use caution when driving or operating machinery.

Accidental substitutions between NovoLog and other insulin products have been reported. Patients should be instructed to always carefully check that they are administering the appropriate insulin to avoid medication errors between NovoLog and any other insulin. The written prescription for NovoLog should be written clearly, to avoid confusion with other insulin products, for example, NovoLog Mix 70/30.

17.2 Patients Using Pumps

Patients using external pump infusion therapy should be trained in intensive insulin therapy with multiple injections and in the function of their pump and pump accessories.

The following insulin pumps† have been used in NovoLog clinical or in vitro studies conducted by Novo Nordisk, the manufacturer of NovoLog:

- Medtronic Paradigm® 512 and 712
- MiniMed 508
- Disetronic® D-TRON® and H-TRON®

Before using another insulin pump with NovoLog, read the pump label to make sure the pump has been evaluated with NovoLog.

NovoLog is recommended for use in any reservoir and infusion sets that are compatible with insulin and the specific pump. Please see recommended reservoir and infusion sets in the pump manual.

To avoid insulin degradation, infusion set occlusion, and loss of the preservative (metacresol), insulin in the reservoir should be replaced at least every 6 days; infusion sets and infusion set insertion sites should be changed at least every 3 days.

Insulin exposed to temperatures higher than 37°C (98.6°F) should be discarded. The temperature of the insulin may exceed ambient temperature when the pump housing, cover, tubing, or sport case is exposed to sunlight or radiant heat. Infusion sites that are erythematous, pruritic, or thickened should be reported to medical personnel, and a new site selected because continued infusion may increase the skin reaction and/or alter the absorption of NovoLog. Pump or infusion set malfunctions or insulin degradation can lead to hyperglycemia and ketosis in a short time because of the small subcutaneous depot of insulin. This is especially pertinent for rapid-acting insulin analogs that are more rapidly absorbed through skin and have shorter duration of action. These differences are particularly relevant when patients are switched from multiple injection therapy. Prompt identification and correction of the cause of hyperglycemia or ketosis is necessary. Problems include pump malfunction, infusion set occlusion, leakage, disconnection or kinking, and degraded insulin. Less commonly, hypoglycemia from pump malfunction may occur. If these problems cannot be promptly corrected, patients should resume therapy with subcutaneous insulin injection and contact their physician [see Dosage and Administration (2), Warnings and Precautions (5) and How Supplied/Storage and Handling (16.2)].

17.3 FDA-Approved Patient Labeling

See separate leaflet.

Rx Only

Date of Issue: March 9, 2013

Version: 20

Novo Nordisk®, NovoLog®, NovoPen® 3, PenFill®, Novolin®, FlexPen®, PenMate® and NovoFine® are registered trademarks of Novo Nordisk A/S.

NovoLog® is covered by US Patent Nos. 5,618,913, 5,866,538, and other patents pending.

FlexPen® is covered by US Patent Nos. 6,582,404, 6,004,297, 6,235,004, and other patents pending.

PenFill® is covered by US Patent No. 5,693,027.

†The brands listed are the registered trademarks of their respective owners and are not trademarks of Novo Nordisk A/S.

© 2002-2013 Novo Nordisk

Manufactured by:

Novo Nordisk A/S

DK-2880 Bagsvaerd, Denmark

For information about NovoLog contact:

Novo Nordisk Inc.

Plainsboro, New Jersey 08536

1-800-727-6500

www.novonordisk-us.com

PATIENT INFORMATION

NovoLog® (NŌ-vō-log)

(insulin aspart [rDNA origin] Injection)

Important:

Know your insulin. Do not change the type of insulin you use unless told to do so by your healthcare provider. The amount of insulin you take as well as the best time for you to take your insulin may need to change if you take a different type of insulin.

Make sure you know the type and strength of insulin prescribed for you.

Read the Patient Information that comes with NovoLog® before you start taking it and each time you get a refill. There may be new information. This leaflet does not take the place of talking with your healthcare provider about your diabetes or your treatment. Make sure you know how to manage your diabetes. Ask your healthcare provider if you have any questions about managing your diabetes.

What is NovoLog®?

NovoLog® is a man-made insulin that is used to control high blood sugar in adults and children with diabetes mellitus.

Who should not use NovoLog®?

Do not take NovoLog® if:

- Your blood sugar is too low (hypoglycemia).
- You are allergic to anything in NovoLog®. See the end of this leaflet for a complete list of ingredients in NovoLog®. Check with your healthcare provider if you are not sure.

Tell your healthcare provider:

- about all of your medical conditions. Medical conditions can affect your insulin needs and your dose of NovoLog®.
- if you are pregnant or breastfeeding. You and your healthcare provider should talk about the best way to manage your diabetes while you are pregnant or breastfeeding. NovoLog® has not been studied in nursing women.
- about all medicines you take, including prescriptions and non-prescription medicines, vitamins and herbal supplements. Your NovoLog® dose may change if you take other medicines.
- if you take any other medicines, especially ones commonly called TZDs (thiazolidinediones).
- if you have heart failure or other heart problems. If you have heart failure, it may get worse while you take TZDs with NovoLog®.

Know the medicines you take. Keep a list of your medicines with you to show your healthcare providers when you get a new medicine.

How should I take NovoLog®?

Only use NovoLog® if it appears clear and colorless. There may be air bubbles. This is normal. If it looks cloudy, thickened, or colored, or if it contains solid particles do not use it and call Novo Nordisk at 1-800-727-6500.

NovoLog® comes in:

- 10 mL vials (small bottles) for use with syringe
- 3 mL PenFill® cartridges for use with the Novo Nordisk 3 mL PenFill® cartridge compatible insulin delivery devices and NovoFine® disposable needles. The cartridge delivery device can be used with a NovoPen® 3 PenMate®
- 3 mL NovoLog® FlexPen®

Read the instructions for use that come with your NovoLog® product. Talk to your healthcare provider if you have any questions. Your healthcare provider should show you how to inject NovoLog® before you start taking it.

- Take NovoLog® exactly as prescribed. You should eat a meal within 5 to 10 minutes after using NovoLog® to avoid low blood sugar.
- NovoLog® is a fast-acting insulin. The effects of NovoLog® start working 10 to 20 minutes after injection or bolus pump infusion.
- Do not inject NovoLog® if you do not plan to eat right after your injection or bolus pump infusion.
- The greatest blood sugar lowering effect is between 1 and 3 hours after the injection or infusion. This blood sugar lowering lasts for 3 to 5 hours.
- While using NovoLog® you may have to change your total dose of insulin, your dose of longer-acting insulin, or the number of injections of longer-acting insulin you use. Pump users given NovoLog® may need to change the amount of total insulin given as a basal infusion.
- Do not mix NovoLog®:
  ∘ with any other insulins when used in a pump
  ∘ with any insulins other than NPH when used with injections by syringe

If your healthcare provider recommends diluting NovoLog®, follow your healthcare provider's instructions exactly so that you know:

- How to make NovoLog® more dilute (that is, a smaller number of units of NovoLog® for a given amount of liquid) and
- How to use this more dilute form of NovoLog®. Do not use dilute insulin in a pump.
- Inject NovoLog® into the skin of your stomach area, upper arms, buttocks or upper legs. NovoLog® may affect your blood sugar levels sooner if you inject it into the skin of your stomach area. Never inject NovoLog® into a vein or into a muscle.
- Change (rotate) your injection site within the chosen area (for example, stomach or upper arm) with each dose. Do not inject into the exact same spot for each injection.
- If you take too much NovoLog®, your blood sugar may fall low (hypoglycemia). You can treat mild low blood sugar (hypoglycemia) by drinking or eating something sugary right away (fruit juice, sugar candies, or glucose tablets). It is important to treat low blood sugar (hypoglycemia) right away because it could get worse and you could pass out (become unconscious). If you pass out you will need help from another person or emergency medical services right away, and will need treatment with a glucagon injection or treatment at a hospital. See “What are the possible side effects of NovoLog®?” for more information on low blood sugar (hypoglycemia).
- If you forget to take your dose of NovoLog®, your blood sugar may go too high (hyperglycemia). If high blood sugar (hyperglycemia) is not treated it can lead to serious problems, like loss of consciousness (passing out), coma or even death. Follow your healthcare provider’s instructions for treating high blood sugar. Know your symptoms of high blood sugar which may include:

- increased thirst
- frequent urination
- drowsiness
- loss of appetite
- a hard time breathing

- fruity smell on the breath
- high amounts of sugar and ketones in your urine
- nausea, vomiting (throwing up) or stomach pain

Check your blood sugar levels. Ask your healthcare provider what your blood sugars should be and when you should check your blood sugar levels.

Your insulin dosage may need to change because of:

- illness
- stress
- other medicines you take

- change in diet
- change in physical activity or exercise

What should I avoid while using NovoLog®?

- Alcohol. Alcohol, including beer and wine, may affect your blood sugar when you take NovoLog®.
- Driving and operating machinery. You may have difficulty concentrating or reacting if you have low blood sugar (hypoglycemia). Be careful when you drive a car or operate machinery. Ask your healthcare provider if it is alright to drive if you often have:
  ∘ low blood sugar
  ∘ decreased or no warning signs of low blood sugar

What are the possible side effects of NovoLog®?

- Low blood sugar (hypoglycemia). Symptoms of low blood sugar may include:

- sweating
- dizziness or lightheadedness
- shakiness
- hunger
- fast heart beat
- tingling of lips and tongue

- trouble concentrating or confusion
- blurred vision
- slurred speech
- anxiety, irritability or mood changes
- headache

Severe low blood sugar can cause unconsciousness (passing out), seizures, and death. Know your symptoms of low blood sugar. Follow your healthcare provider’s instructions for treating low blood sugar. Talk to your healthcare provider if low blood sugar is a problem for you.

- Serious allergic reaction (whole body reaction). Get medical help right away, if you develop a rash over your whole body, have trouble breathing, a fast heartbeat, or sweating.
- Reactions at the injection site (local allergic reaction). You may get redness, swelling, and itching at the injection site. If you keep having skin reactions or they are serious talk to your healthcare provider. You may need to stop using NovoLog® and use a different insulin. Do not inject insulin into skin that is red, swollen, or itchy.
- Skin thickens or pits at the injection site (lipodystrophy). Change (rotate) where you inject your insulin to help to prevent these skin changes from happening. Do not inject insulin into this type of skin.
- Swelling of your hands and feet
- Heart Failure. Taking certain diabetes pills called thiazolidinediones or “TZDs” with NovoLog® may cause heart failure in some people. This can happen even if you have never had heart failure or heart problems before. If you already have heart failure it may get worse while you take TZDs with NovoLog®. Your healthcare provider should monitor you closely while you are taking TZDs with NovoLog®. Tell your healthcare provider if you have any new or worse symptoms of heart failure including:
  ∘ shortness of breath
  ∘ swelling of your ankles or feet
  ∘ sudden weight gain
Treatment with TZDs and NovoLog® may need to be adjusted or stopped by your healthcare provider if you have new or worse heart failure.
- Vision changes
- Low potassium in your blood (hypokalemia)
- Weight gain

These are not all of the possible side effects from NovoLog®. Ask your healthcare provider or pharmacist for more information.

Call your healthcare provider for medical advice about side effects. You may report side effects to FDA at 1-800-FDA-1088.

How should I store NovoLog®?

All Unopened NovoLog®:

- Keep all unopened NovoLog® in the refrigerator between 36° to 46°F (2° to 8°C).
- Do not freeze. Do not use NovoLog® if it has been frozen.
- Keep unopened NovoLog® in the carton to protect from light.

NovoLog® in use:

- Vials
  ∘ Keep in the refrigerator or at room temperature below 86°F (30°C) for up to 28 days.
  ∘ Keep vials away from direct heat or light.
  ∘ Throw away an opened vial after 28 days of use, even if there is insulin left in the vial.
  ∘ Do not draw up NovoLog® into a syringe and store for later use.
  ∘ Unopened vials can be used until the expiration date on the NovoLog® label, if the medicine has been stored in a refrigerator.
- PenFill® Cartridges or NovoLog® FlexPen®
  ∘ Keep at room temperature below 86°F (30°C) for up to 28 days.
  ∘ Do not store a PenFill® cartridge or NovoLog® FlexPen® that you are using in the refrigerator.
  ∘ Keep PenFill® cartridges and NovoLog® FlexPen® away from direct heat or light.
  ∘ Throw away a used PenFill® cartridge or NovoLog® FlexPen® after 28 days, even if there is insulin left in the cartridge or syringe.
- NovoLog® in the pump reservoir and the complete external pump infusion set
  ∘ The infusion set and the infusion site should be changed at least every 3 days. The insulin in the reservoir should be changed at least every 6 days even if you have not used all of the insulin. Change the infusion set and the infusion site more often than every 3 days if you have high blood sugar (hyperglycemia), the pump alarm sounds, or the insulin flow is blocked (occlusion).

General advice about NovoLog®

Medicines are sometimes prescribed for conditions that are not mentioned in the patient leaflet. Do not use NovoLog® for a condition for which it was not prescribed. Do not give NovoLog® to other people, even if they have the same symptoms you have. It may harm them.

This leaflet summarizes the most important information about NovoLog®. If you would like more information about NovoLog® or diabetes, talk with your healthcare provider. You can ask your healthcare provider or pharmacist for information about NovoLog® that is written for healthcare professionals. Call 1-800-727-6500 or visit www.novonordisk-us.com for more information.

Helpful information for people with diabetes is published by the American Diabetes Association, 1701 N Beauregard Street, Alexandria, VA 22311 and on www.diabetes.org.

NovoLog® ingredients include:

- insulin aspart
- glycerin
- phenol
- metacresol

- zinc
- disodium hydrogen phosphate dihydrate
- sodium chloride
- water for injection

All NovoLog® vials, PenFill® cartridges and NovoLog® FlexPen® are latex free.

Date of Issue: March 9, 2013

Version: 12

Novo Nordisk®, NovoLog®, PenFill®, FlexPen®, NovoPen®, NovoFine®, and PenMate® are registered trademarks of Novo Nordisk A/S.

NovoLog® is covered by US Patent Nos. 5,618,913, 5,866,538, and other patents pending.

FlexPen® is covered by US Patent Nos. 6,582,404, 6,004,297, 6,235,004, and other patents pending.

PenFill® is covered by US Patent No. 5,693,027.

© 2002-2013 Novo Nordisk

Manufactured by:

Novo Nordisk A/S

DK-2880 Bagsvaerd, Denmark

For information about NovoLog® contact:

Novo Nordisk Inc.

800 Scudders Mill Road

Plainsboro, New Jersey 08536

PATIENT INSTRUCTIONS FOR USE

NovoLog® (NŌ-vō-log)

(insulin aspart [rDNA origin] injection)

10 mL vial (100 Units/mL, U-100)

Read this Instructions for Use before you start taking NovoLog® and each time you get a refill. There may be new information. This information does not take the place of talking to your healthcare provider about your medical condition or your treatment.

Supplies you will need to give your NovoLog® injection:

- 10 mL NovoLog® vial
- insulin syringe and needle
- alcohol swab

Preparing your NovoLog® dose:

- Wash your hands with soap and water.
- Before you start to prepare your injection, check the NovoLog® label to make sure that you are taking the right type of insulin. This is especially important if you use more than 1 type of insulin.
- NovoLog® should look clear and colorless. Do not use NovoLog® if it is thick, cloudy, or is colored.
- Do not use NovoLog® past the expiration date printed on the label.

Step 1: Pull off the tamper resistant cap (See Figure A).

Step 2: Wipe the rubber stopper with an alcohol swab (See Figure B).

Step 3: Hold the syringe with the needle pointing up.Pull down on the plunger until the black tip reaches the line for the number of units for your prescribed dose (See Figure C).

Step 4: Push the needle through the rubber stopper of the NovoLog® vial (See Figure D).

Step 5: Push the plunger all the way in. This puts air into the NovoLog® vial (See Figure E).

Step 6: Turn the NovoLog® vial and syringe upside down and slowly pull the plunger down until the black tip is a few units past the line for your dose (See Figure F).

- If there are air bubbles, tap the syringe gently a few times to let any air bubbles rise to the top (See Figure G).

Step 7: Slowly push the plunger up until the black tip reaches the line for your NovoLog® dose (See Figure H).

Step 8: Check the syringe to make sure you have the right dose of NovoLog®.

Step 9: Pull the syringe out of the vial’s rubber stopper (See Figure I).

Giving your Injection:
- Inject your NovoLog® exactly as your healthcare provider has shown you. Your healthcare provider should tell you if you need to pinch the skin before injecting.
- NovoLog® can be injected under the skin (subcutaneously) of your stomach area, buttocks, upper legs or upper arms, infused in an insulin pump, or given through a needle in your arm (intravenously) by your healthcare provider.
- If you inject NovoLog®,change (rotate) your injection sites within the area you choose for each dose. Do not use the same injection site for each injection.
- If you use NovoLog® in an insulin pump, you should change your insertion site every 3 days. The insulin in the reservoir should be changed at least every 6 days even if you have not used all of the insulin.
- If you use NovoLog® in an insulin pump, see your insulin pump manual for instructions or talk to your healthcare provider.
- NPH insulin is the only type of insulin that can be mixed with NovoLog®. Do not mix NovoLog® with any other type of insulin.
- NovoLog® should only be mixed with NPH insulin if it is going to be injected right away under your skin (subcutaneously).
- NovoLog® should be drawn up into the syringe before you draw up your NPH insulin.
- Talk to your healthcare provider if you are not sure about the right way to mix NovoLog® and NPH insulin.

Step 10: Choose your injection site and wipe the skin with an alcohol swab. Let the injection site dry before you inject your dose (See Figure J).

Step 11: Insert the needle into your skin. Push down on the plunger to inject your dose (See Figure K). Needle should remain in the skin for at least 6 seconds to make sure you have injected all the insulin.

Step 12: Pull the needle out of your skin. After that, you may see a drop of NovoLog® at the needle tip. This is normal and does not affect the dose you just received (See Figure L).

- If you see blood after you take the needle out of your skin, press the injection site lightly with a
piece of gauze or an alcohol swab. Do not rub the area.

After your injection:

- Do not recap the needle. Recapping the needle can lead to a needle stick injury.
- Throw away empty insulin vials, used syringes, and needles in a sharps container or some type of hard plastic or metal container with a screw on cap such as a detergent bottle or empty coffee can. Check with your healthcare provider about the right way to throw away the container. There may be local or state laws about how to throw away used syringes and needles. Do not throw away used syringes and needles in household trash or recycling bins.

How should I store NovoLog®?

Do not freeze NovoLog®. Do not use NovoLog® if it has been frozen.

- Keep NovoLog® away from heat or light.
- Store opened and unopened NovoLog® vials in the refrigerator at 36OF to 46OF (2OC to 8OC). Opened NovoLog® vials can also be stored out of the refrigerator below 86OF (30OC).
- Unopened vials may be used until the expiration date printed on the label, if they are kept in the refrigerator.
- Opened NovoLog® vials should be thrown away after 28 days, even if they still have insulin left in them.

General information about the safe and effective use of NovoLog®

- Always use a new syringe and needle for each injection.
- Do not share syringes or needles.
- Keep NovoLog® vials, syringes, and needles out of the reach of children.

This Instructions for Use has been approved by the U.S. Food and Drug Administration.

Manufactured by:

Novo Nordisk A/S

DK-2880 Bagsvaerd, Denmark

NovoLog® is a registered trademark of Novo Nordisk A/S.

NovoLog® is covered by US Patent Nos. 5,618,913, 5,866,538, and other patents pending.

© 2002-2013 Novo Nordisk

For information about NovoLog® contact:

Novo Nordisk Inc.

800 Scudders Mill Road

Plainsboro, New Jersey 08536

1-800-727-6500

www.novonordisk-us.com

Revised: March 2013

PATIENT INSTRUCTIONS FOR USE

NovoLog® 3 mL PenFill® cartridge (100 Units/mL, U-100)

Before using the NovoLog® cartridge

1. Talk with your healthcare provider for information about where to inject NovoLog® (injection sites) and how to give an injection with your insulin delivery device.
2. Read the instruction manual that comes with your insulin delivery device for complete instructions on how to use the PenFill® cartridge with the device.

How to use the NovoLog® cartridge

1. Check your insulin. Just before using your NovoLog® cartridge, check to make sure that you have the right type of insulin. This is especially important if you use different types of insulin.
2. Carefully look at the cartridge and the insulin inside it. The insulin should be clear and colorless. The tamper-resistant foil should be in place before the first use. If the foil has been broken or removed before your first use of the cartridge, or if the insulin is cloudy or colored, do not use it. Call Novo Nordisk at 1-800-727-6500.
3. Wash your hands well with soap and water. If you clean your injection site with an alcohol swab, let the injection site dry before you inject. Talk with your healthcare provider for guidance on injection sites and how to give an injection with your insulin delivery device.
4. Gather your supplies for injecting NovoLog®.
5. Insert a 3 mL cartridge into your Novo Nordisk 3 mL PenFill® cartridge compatible insulin delivery device. Wipe the front rubber stopper of the 3 mL PenFill® cartridge with an alcohol swab, then attach a new needle. For NovoFine® needles, remove the big outer needle cap and the inner needle cap. Always use a new needle for each injection to prevent infection.

Giving the airshot before each injection:

To prevent the injection of air and to make sure insulin is delivered, you must do an airshot before each injection. Hold the device with the needle pointing up and gently tap the PenFill® cartridge holder with your finger a few times to raise any air bubbles to the top of the cartridge. Do the airshot as described in the device instruction manual.

Giving the injection

6. Dial the number of units on the insulin delivery device that you need to inject. Inject the right way as shown to you by your healthcare provider.

7. Insert the needle into the skin. Inject the dose by pressing the push button all the way in. Keep the needle in the skin for at least 6 seconds, and keep the push button pressed all the way in until the needle has been pulled out from the skin. This will make sure that the full dose has been given. You may see a drop of NovoLog® at the needle tip. This is normal and has no effect on the dose you just received. If blood appears after you take the needle out of your skin, press the injection site lightly with a finger. Do not rub the area.

After the injection

8. Do not recap the needle. Recapping can lead to a needle stick injury.

9. Remove the needle from the PenFill® cartridge after each injection. Keep the 3 mL PenFill® cartridge in the insulin delivery device. The needle should not be attached to the 3 mL PenFill® cartridge during storage. This will prevent infection or leakage of insulin and will help ensure that you receive the right dose of NovoLog®.

10. Put the used needle and cartridge in a sharps container, or some type of hard plastic or metal container with a screw on top such as a detergent bottle or coffee can. Check with your healthcare provider about the right way to throw away used needles and cartridges. There may be local or state laws about how to throw away used needles and syringes. Do not throw used needles and cartridges in household trash or recycling bins.

11. Put the pen cap back on the Novo Nordisk 3 mL PenFill® cartridge compatible insulin delivery device.

Date of Issue: March 2013

Version: 9

Novo Nordisk®, NovoLog®, PenFill®, and NovoFine® are registered trademarks of Novo Nordisk A/S.

NovoLog® is covered by US Patent Nos. 5,618,913, 5,866,538, and other patents pending.

PenFill® is covered by US Patent No. 5,693,027.

© 2002-2013 Novo Nordisk

Manufactured by:

Novo Nordisk A/S

DK-2880 Bagsvaerd, Denmark

For information about NovoLog® contact:

Novo Nordisk Inc.

800 Scudders Mill Road

Plainsboro, New Jersey 08536

PATIENT INSTRUCTIONS FOR USE

NovoLog® FlexPen®

Introduction

Please read the following instructions carefully before using your NovoLog® FlexPen®.

NovoLog FlexPen is a disposable dial-a-dose insulin pen. You can select doses from 1 to 60 units in increments of 1 unit. NovoLog FlexPen is designed to be used with NovoFine® needles.

Δ NovoLog FlexPen should not be used by people who are blind or have severe visual problems without the help of a person who has good eyesight and who is trained to use the NovoLog FlexPen the right way.

Getting ready

Make sure you have the following items:

- NovoLog FlexPen
- New NovoFine needle
- Alcohol swab

Preparing Your NovoLog FlexPen

Wash your hands with soap and water. Before you start to prepare your injection, check the label to make sure that you are taking the right type of insulin. This is especially important if you take more than 1 type of insulin. NovoLog should look clear.

A. Pull off the pen cap (see diagram A).

Wipe the rubber stopper with an alcohol swab.

B. Attaching the needle

Remove the protective tab from a disposable needle.

Screw the needle tightly onto your FlexPen. It is important that the needle is put on straight (see diagram B).

Never place a disposable needle on your NovoLog FlexPen until you are ready to take your injection.

C. Pull off the big outer needle cap (see diagram C).

D. Pull off the inner needle cap and dispose of it (see diagram D).

Δ Always use a new needle for each injection to help ensure sterility and prevent blocked needles.
Δ Be careful not to bend or damage the needle before use.
Δ To reduce the risk of unexpected needle sticks, never put the inner needle cap back on the needle.

Giving the airshot before each injection

Before each injection small amounts of air may collect in the cartridge during normal use. To avoid injecting air and to ensure proper dosing:

E. Turn the dose selector to select 2 units (see diagram E).

F. Hold your NovoLog FlexPen with the needle pointing up. Tap the cartridge gently with your finger a few times to make any air bubbles collect at the top of the cartridge (see diagram F).

G. Keep the needle pointing upwards, press the push-button all the way in (see diagram G). The dose selector returns to 0.

A drop of insulin should appear at the needle tip. If not, change the needle and repeat the procedure no more than 6 times.

If you do not see a drop of insulin after 6 times, do not use the NovoLog FlexPen and contact Novo Nordisk at 1-800-727-6500.

A small air bubble may remain at the needle tip, but it will not be injected.

Selecting your dose

Check and make sure that the dose selector is set at 0.

H. Turn the dose selector to the number of units you need to inject. The pointer should line up with your dose.

The dose can be corrected either up or down by turning the dose selector in either direction until the correct dose lines up with the pointer (see diagram H). When turning the dose selector, be careful not to press the push-button as insulin will come out.

You cannot select a dose larger than the number of units left in the cartridge.

You will hear a click for every single unit dialed. Do not set the dose by counting the number of clicks you hear.

Δ Do not use the cartridge scale printed on the cartridge to measure your dose of insulin.

Giving the injection

Do the injection exactly as shown to you by your healthcare provider. Your healthcare provider should tell you if you need to pinch the skin before injecting.

I. Insert the needle into your skin.

Inject the dose by pressing the push-button all the way in until the 0 lines up with the pointer (see diagram I). Be careful only to push the button when injecting.

Turning the dose selector will not inject insulin.

J. Keep the needle in the skin for at least 6 seconds, and keep the push-button pressed all the way in until the needle has been pulled out from the skin (see diagram J). This will make sure that the full dose has been given.

You may see a drop of NovoLog at the needle tip. This is normal and has no effect on the dose you just received. If blood appears after you take the needle out of your skin, press the injection site lightly with a finger. Do not rub the area.

After the injection

Do not recap the needle. Recapping can lead to a needle stick injury. Remove the needle from the NovoLog FlexPen after each injection. This helps to prevent infection, leakage of insulin, and will help to make sure you inject the right dose of insulin.

Δ Put the needle and any empty NovoLog FlexPen or any used NovoLog FlexPen still containing insulin in a sharps container or some type of hard plastic or metal container with a screw top such as a detergent bottle or empty coffee can. These containers should be sealed and thrown away the right way. Check with your healthcare provider about the right way to throw away used syringes and needles. There may be local or state laws about how to throw away used needles and syringes. Do not throw away used needles and syringes in household trash or recycling bins.

The NovoLog FlexPen prevents the cartridge from being completely emptied. It is designed to deliver 300 units.

K. Put the pen cap on the NovoLog FlexPen and store the NovoLog FlexPen without the needle attached (see diagram K).

Function Check

L. If your NovoLog FlexPen is not working the right way, follow the steps below:

- Screw on a new NovoFine needle.
- Remove the big outer needle cap and the inner needle cap.
- Do an airshot as described in "Giving the airshot before each injection".
- Put the big outer needle cap onto the needle. Do not put on the inner needle cap.
- Turn the dose selector so the dose indicator window shows 20 units.
- Hold the NovoLog FlexPen so the needle is pointing down.
- Press the push-button all the way in.

The insulin should fill the lower part of the big outer needle cap (see diagram L). If the NovoLog FlexPen has released too much or too little insulin, do the function check again. If the same problem happens again, do not use your NovoLog FlexPen and contact Novo Nordisk at 1-800-727-6500.

Maintenance

Your FlexPen is designed to work accurately and safely. It must be handled with care. Avoid dropping your FlexPen as it may damage it. If you are concerned that your FlexPen is damaged, use a new one. You can clean the outside of your FlexPen by wiping it with a damp cloth. Do not soak or wash your FlexPen as it may damage it. Do not refill your FlexPen.

Δ Remove the needle from the NovoLog FlexPen after each injection. This helps to ensure sterility, prevent leakage of insulin, and will help to make sure you inject the right dose of insulin for future injections.

Δ Be careful when handling used needles to avoid needle sticks and transfer of infectious diseases.

Δ Keep your NovoLog FlexPen and needles out of the reach of children.

Δ Use NovoLog FlexPen as directed to treat your diabetes. Needles and NovoLog FlexPen must not be shared.

Δ Always use a new needle for each injection.

Δ Novo Nordisk is not responsible for harm due to using this insulin pen with products not recommended by Novo Nordisk.

Δ As a precautionary measure, always carry a spare insulin delivery device in case your NovoLog FlexPen is lost or damaged.

Δ Remember to keep the disposable NovoLog FlexPen with you. Do not leave it in a car or other location where it can get too hot or too cold.

PRINCIPAL DISPLAY PANEL - 3 mL NovoLog FlexPen

NDC 68258-8899-03

NovoLog® FlexPen®

Prefilled Syringe

Insulin aspart Injection (rDNA origin)

100 units/mL (U-100)

5 x 3 mL Prefilled Insulin Syringes

Rx only

Single patient use only

For use with NovoFine® disposable needles.

Keep in a cold place. Avoid freezing.

Protect from light.